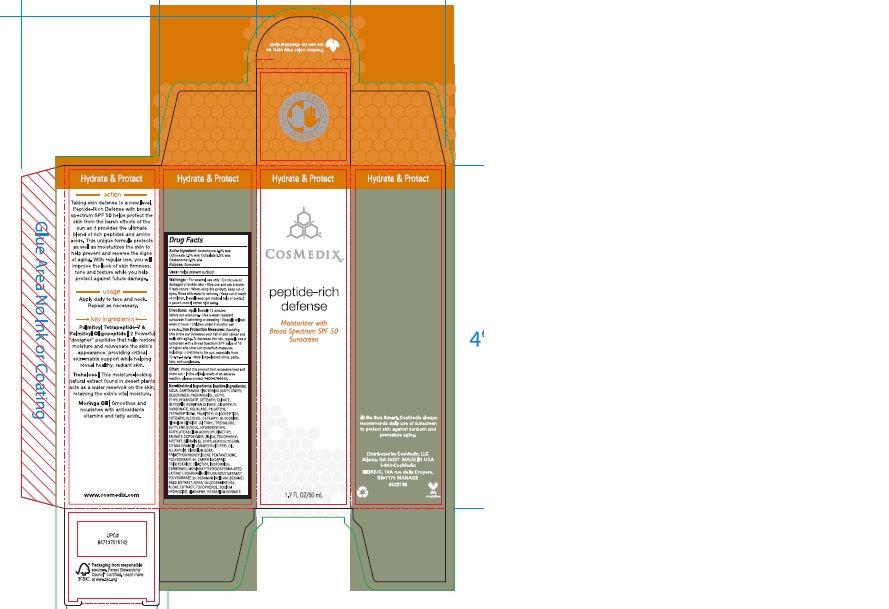 DRUG LABEL: Cosmedix SPF50
NDC: 61531-103 | Form: EMULSION
Manufacturer: Universal Packaging Systems, Inc. DBA: PakLab
Category: otc | Type: HUMAN OTC DRUG LABEL
Date: 20191227

ACTIVE INGREDIENTS: OXYBENZONE 0.05 g/1 g; OCTINOXATE 0.075 g/1 g; AVOBENZONE 0.03 g/1 g; OCTISALATE 0.05 g/1 g
INACTIVE INGREDIENTS: GLYCERIN

ACTIVE INGREDIENT

Avobenzone 3.0%

Octinoxate 7.5%

Octisalate 5.0%

Oxybenzone 5.0%

PURPOSE

Helps prevent sunburn

INSTRUCTIONS FOR USE

Apply liberally 15 minutes before sun exposure.

INACTIVE INGREDIENT

Water (Aqua), Propanediol, Dicaprylyl Carbonate, Carthamus Tinctorius (Safflower) Oleosomes, Cetyl Ethylhexanoate, Glycerin, Cetearyl Olivate, Squalane, Sorbitan Olivate, Silica, Trehalose, Trimethoxybenzylidene Pentanedione, Hydroxyethyl Acrylate/Sodium Acryloyldimethyl Taurate Copolymer, Butylene Glycol, Cetearyl Alcohol, Cetearyl Glucoside, Tocopheryl Acetate, Ethylhexylglycerin, Citrus Grandis (Grapefruit) Peel Oil, Limonene, Potassium Sorbate, Polysorbate 60, Allantoin, Disodium EDTA, Titanium Dioxide (CI 77891), Caprylic/Capric Triglyceride, Sodium Hydroxide, Dimethyl Isosorbide, Carbomer, Moringa Pterygosperma Seed Extract, Boerhavia Diffusa Root Extract, Polysorbate 20, Sesamum Indicum (Sesame) Seed Extract, Urea, Glucosamine HCl, Algae Extract, Palmitoyl Oligopeptide, Tocopherol, Palmitoyl Tetrapeptide-7.

QUESTIONS

In the unlikely event of an adverse reaction, please contact 1-800-676-9522

WARNINGS

For external use only. Do not use on damaged or broken skin. Stop use and ask a doctor if rash occurs.

INDICATIONS AND USAGE

Helps protect against sunburn.

DOSAGE AND ADMINISTRATION

Topical emulsion